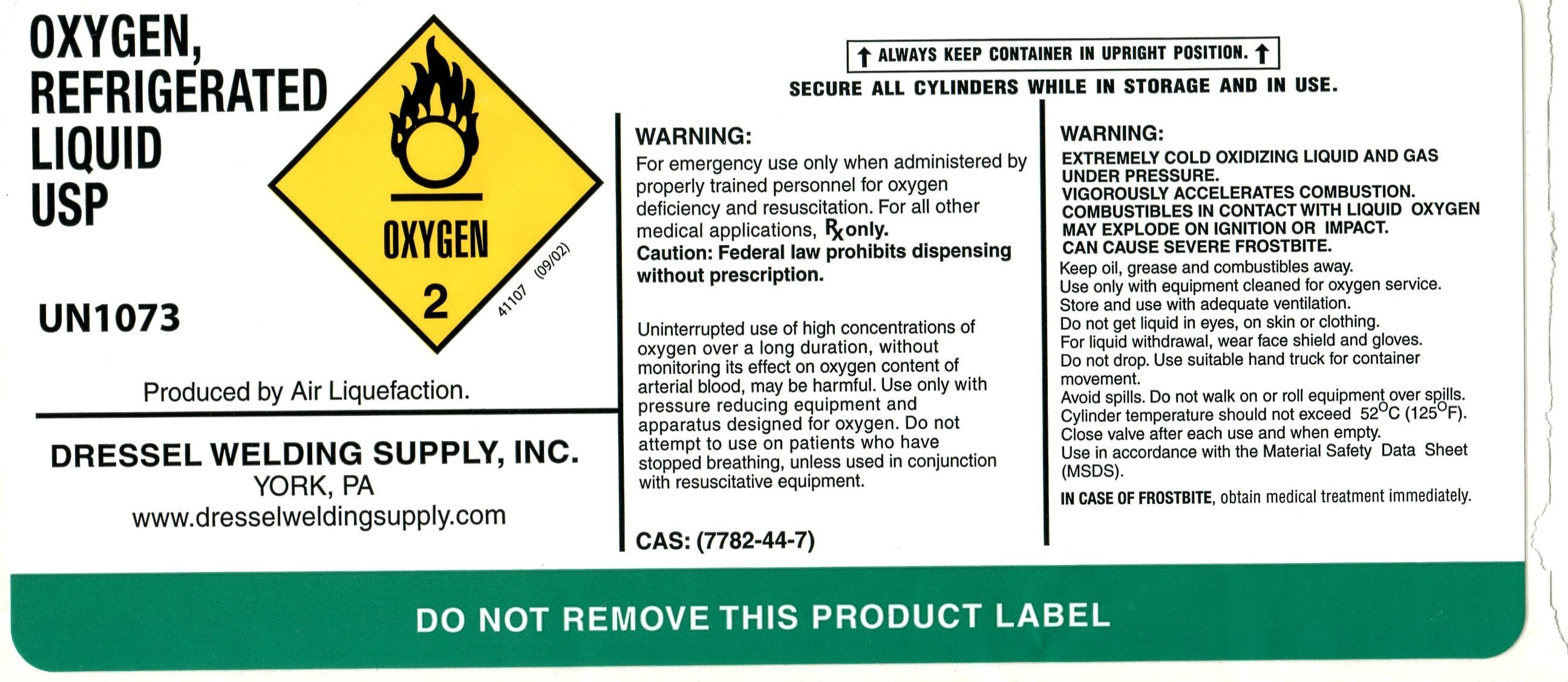 DRUG LABEL: Oxygen
NDC: 52072-002 | Form: LIQUID
Manufacturer: Dressel Welding Supply, Inc.
Category: prescription | Type: HUMAN PRESCRIPTION DRUG LABEL
Date: 20091222

ACTIVE INGREDIENTS: Oxygen 992 L/1000 L

Liquid Oxygen Label

PACKAGE LABEL

Oxygen, Refrigerated Liquid USP UN1073 Produced by Air Liquefaction. Dressel Welding Supply, Inc. York, PA www.dresselweldingsupply.com Always keep container in upright position. Secure all cylinders while in storage and in use. Warning: For emergency use only when administered by properly trained personnel for oxygen deficiency and resuscitation. For all other medical applications, Rx only. Caution: Federal law prohibits dispensing without a prescription. Uninterrupted use of high concentrations of oxygen over a long duration, without monitoring its effect on oxygen content of arterial blood, may be harmful. Use only with pressure reducing equipment and apparatus designed for oxygen. Do not attempt to use on patients who have stopped breathing, unless used in conjunction with resuscitative equipment. CAS (7782-44-7) Warning: Extremely cold oxidizing liquid and gas under pressure. Vigorously accelerates combustion. Combustibles in contact with liquid oxygen may explode on ignition or impact. Can cause severe frostbite. Keep oil, grease and combustibles away. Use only with equipment cleaned for oxygen service. Store and use adequate ventilation. Do not get liquid in eyes, on skin or clothing. For liquid withdrawal, wear face shield and gloves. Do not drop. Use suitable hand truck for container movement. Avoid spills. Do not walk on or roll equipment over spills. Cylinder temperature should not exceed 52 degrees C (125 degrees F). Close valve after each use and when empty. Use in accordance with the Material Safety Data Sheet (MSDS). In case of frostbite, obtain medical treatment immediately. Do not remove this product label.